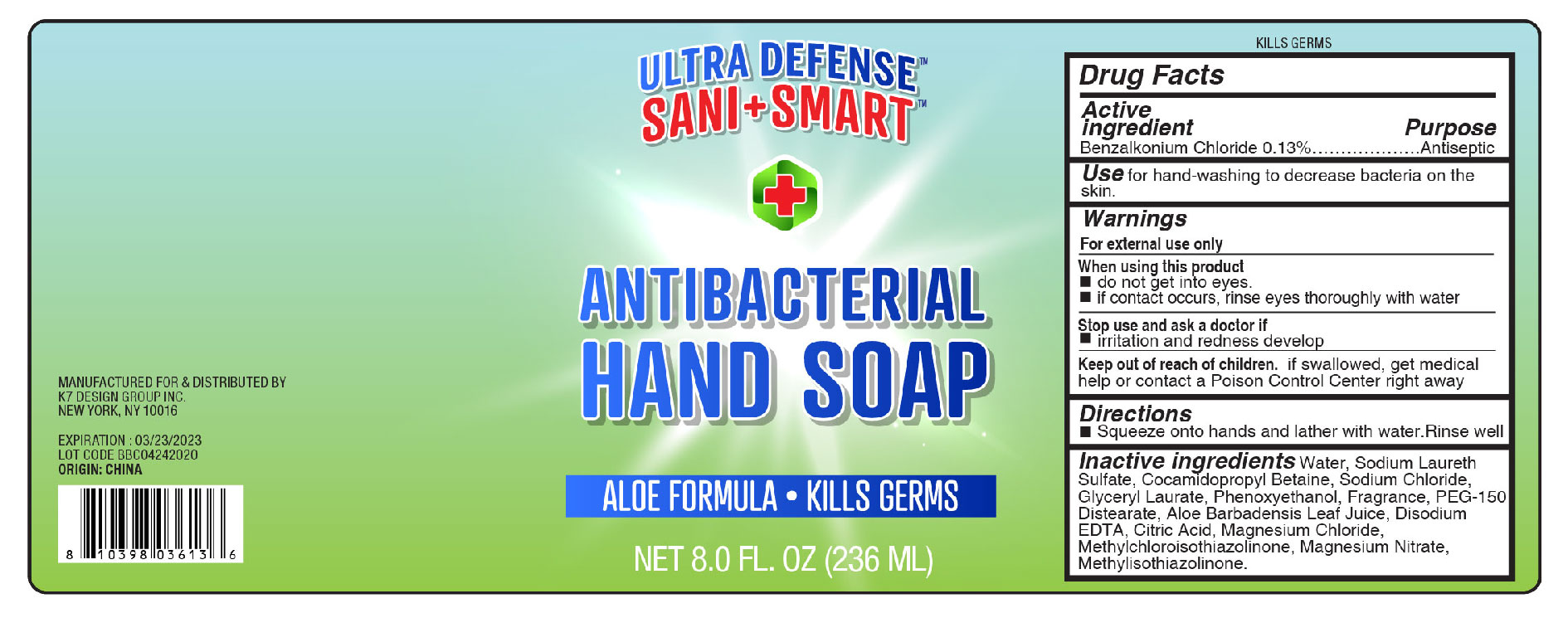 DRUG LABEL: SANI SMART Aloe Formula
NDC: 74177-002 | Form: SOAP
Manufacturer: K7 Design Group Inc.
Category: otc | Type: HUMAN OTC DRUG LABEL
Date: 20200427

ACTIVE INGREDIENTS: BENZALKONIUM CHLORIDE 0.13 g/100 mL
INACTIVE INGREDIENTS: METHYLISOTHIAZOLINONE; ANHYDROUS CITRIC ACID; PHENOXYETHANOL; PEG-150 DISTEARATE; EDETATE DISODIUM; MAGNESIUM NITRATE; COCAMIDOPROPYL BETAINE; ALOE VERA LEAF; MAGNESIUM CHLORIDE; METHYLCHLOROISOTHIAZOLINONE; SODIUM CHLORIDE; WATER; GLYCERYL LAURATE; SODIUM LAURETH SULFATE

SANI SMART Antibacterial Hand Soap

Active Ingredient

Benzalkonium Chloride 0.13%

Purpose

Antiseptic

Use

for hand-washing to decrease bacteria on the skin.

Warnings

For external use only

When using this product

■ do not get into eyes.

■ if contact occurs, rinse eyes thoroughly with water.

Stop use and ask a doctor if

■ irritation and redness develops

Keep out of reach of children

If swallowed, get medical help or contact a Poison Control Center right away.

Directions

■ Squeeze into hands and lather with water. Rinse well

Inactive ingredients

Water, Sodium Laureth Sulfate, Cocamidopropyl Betaine, Sodium Chloride, Glyceryl Laurate, Phenoxyethanol, Fragrance, PEG-150 Distearate, Aloe Barbadensis Leaf Juice, Disodium EDTA, Citric Acid, Magnesium Chloride, Methylchloroisothiazolinone, Magnesium Nitrate, Methylisothiazolinone